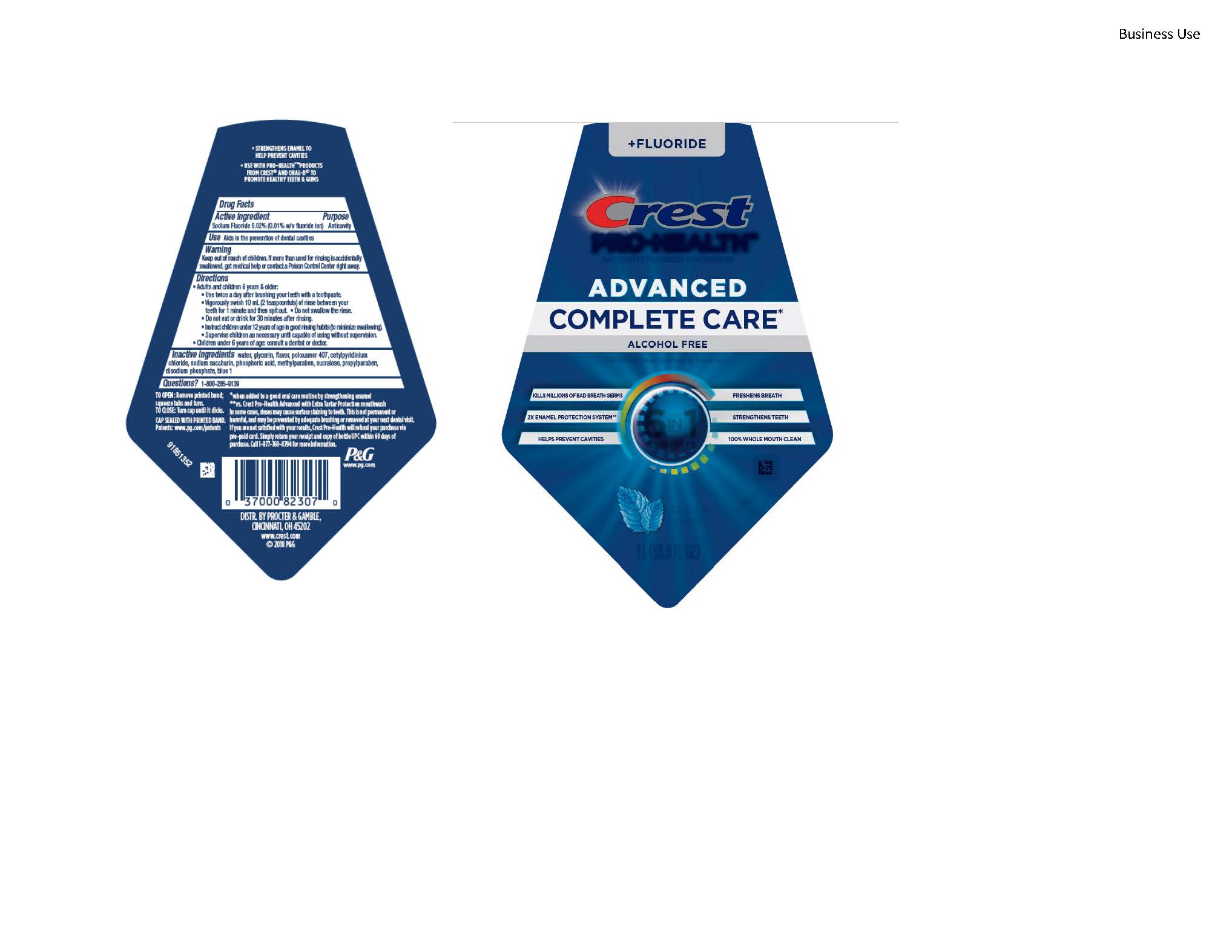 DRUG LABEL: Crest Pro-Health Advanced Complete Care
NDC: 69423-751 | Form: RINSE
Manufacturer: The Procter & Gamble Manufacturing Company
Category: otc | Type: HUMAN OTC DRUG LABEL
Date: 20260108

ACTIVE INGREDIENTS: SODIUM FLUORIDE 0.1 mg/1 mL
INACTIVE INGREDIENTS: METHYLPARABEN; SUCRALOSE; CETYLPYRIDINIUM CHLORIDE; PROPYLPARABEN; FD&C BLUE NO. 1; POLOXAMER 407; WATER; GLYCERIN; PHOSPHORIC ACID; SACCHARIN SODIUM; SODIUM PHOSPHATE, DIBASIC, ANHYDROUS

Crest Pro Health Advanced Complete Care

Drug Facts

Active ingredient

Sodium Fluoride 0.02% (0.01% w/v fluoride ion)

Purpose

Anticavity

Use

Aids in the prevention of dental cavities

Warnings

Keep out of reach of children. If more than used for rinsing is accidentally swallowed, get medical help or contact a Poison Control Center right away.

Directions

- Adults and children 6 years & older: Use twice a day after brushing your teeth with a toothpaste.
- Vigorously swish the 10 mL of rinse between your teeth for 1 minute and then spit out.
- Do not swallow the rinse.
- Do not eat or drink for 30 minutes after rinsing.
- Instruct children under 12 years of age in good rinsing habits (to minimize swallowing).
- Supervise children as necessary until capable of using without supervision.
- Children under 6 years of age: Consult a dentist or doctor.

Inactive ingredients

water, glycerin, flavor, poloxamer 407, cetylpyridinium chloride, sodium saccharin, phosphoric acid, methylparaben, sucralose, propylparaben,
disodium phosphate, blue 1

Questions?

1-800-285-9139

DISTR. BY
PROCTER & GAMBLE,
CINCINNATI, OH 45202

Crest Pro Heath Advanced Complete Care 1L

Crest

Pro-Health

Anticavity Fluoride Mouthwash

Advanced

Complete Care*

Alchol Free

IMPORTANT: Read directions for proper use.

6 in 1 Benefits

KILLS MILLIONS OF BAD BREATH GERMS

FRESHENS BREATH

2X ENAMEL PROTECTION SYSTEM**
HELPS PREVENT CAVITIES

STRENGTHENS TEETH

100% WHOLE MOUTH CLEAN

CLEAN MINT

1L (33.8 FL OZ)